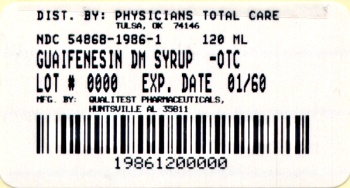 DRUG LABEL: Guaifenesin
NDC: 54868-1986 | Form: SYRUP
Manufacturer: Physicians Total Care, Inc.
Category: otc | Type: HUMAN OTC DRUG LABEL
Date: 20120301

ACTIVE INGREDIENTS: DEXTROMETHORPHAN HYDROBROMIDE 10 mg/5 mL; GUAIFENESIN 100 mg/5 mL
INACTIVE INGREDIENTS: CITRIC ACID MONOHYDRATE; FD&C RED NO. 40; GLYCERIN; HIGH FRUCTOSE CORN SYRUP; GLUCOSE OXIDASE; WATER; SACCHARIN SODIUM; SODIUM BENZOATE

Q-Tussin DM 0855

Active ingredients (in each 5 mL = 1 tsp)

Dextromethorphan HBr, USP 10 mg

Guaifenesin, USP 100 mg

Purpose

Cough suppressant

Expectorant

Uses

- temporarily relieves cough due to minor throat and bronchial irritation as may occur with a cold
- helps loosen phlegm (mucus) and thin bronchial secretions to drain bronchial tubes

Warnings

Do not use if you are now taking a prescription monoamine oxidase inhibitor (MAOI) (certain drugs for depression, psychiatric or emotional conditions, or Parkinson’s disease), or for 2 weeks after stopping the MAOI drug. If you do not know if your prescription drug contains an MAOI, ask a doctor or pharmacist before taking this product.

Ask a doctor before use if you have

- cough that occurs with too much phlegm (mucus)
- cough that lasts or is chronic such as occurs with smoking, asthma, chronic bronchitis, or emphysema

Stop use and ask a doctor if cough lasts more than 7 days, comes back or is accompanied by fever, rash, or persistent headache.

These could be signs of a serious condition.

PREGNANCY OR BREAST FEEDING

If pregnant or breast-feeding, ask a health professional before use.

Keep out of reach of children.

In case of overdose, get medical help or contact a Poison Control Center right away.

Directions

- do not take more than 6 doses in any 24-hour period
- this adult product is not intended for use in children under 12 years of age

age (yr) | dose (tsp)
adults and children 12 years and over | 2 teaspoons every 4 hours
children under 12 years | do not use

Other information

- store at 15° to 30°C (59° to 86°F)
- dosage cup provided

You may report serious side effects to: 130 Vintage Drive, Huntsville, AL 35811.

Inactive ingredients

citric acid, FD&C red #40, flavors, glycerin, high fructose corn syrup, liquid glucose, purified water, saccharin sodium, sodium benzoate

Made in the USA
for Qualitest Pharmaceuticals
Huntsville, AL 35811

Rev. 7/09 R4
8281171 0855

Additional barcode labeling by:
Physicians Total Care, Inc.
Tulsa, Oklahoma 74146

PRINCIPAL DISPLAY PANEL

NDC 54868-1986-1
118 mL